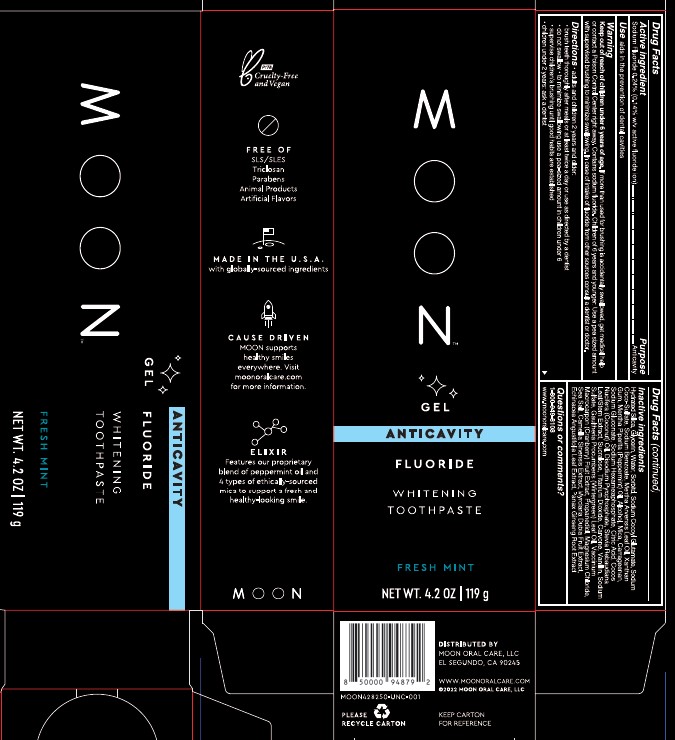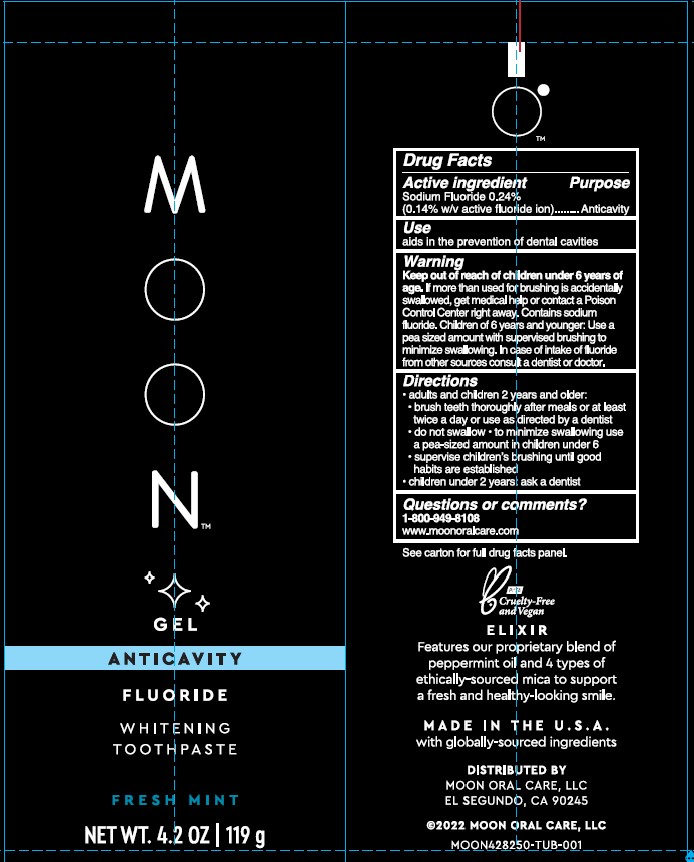 DRUG LABEL: Moon Whitening Gel Anticavity
NDC: 82214-004 | Form: GEL, DENTIFRICE
Manufacturer: Moon Oral Care, LLC
Category: otc | Type: HUMAN OTC DRUG LABEL
Date: 20231212

ACTIVE INGREDIENTS: SODIUM FLUORIDE 0.24 g/100 g
INACTIVE INGREDIENTS: MAGNESIUM CHLORIDE; SODIUM POLYMETAPHOSPHATE; CITRIC ACID MONOHYDRATE; SODIUM ACID PYROPHOSPHATE; TITANIUM DIOXIDE; MYRCIARIA DUBIA FRUIT; WATER; SODIUM BENZOATE; MICA; SODIUM GLUCONATE; SORBITOL; SODIUM COCO-SULFATE; MENTHA ARVENSIS LEAF OIL; SODIUM SULFATE; SODIUM COCOYL GLUTAMATE; SUCRALOSE; COCONUT OIL; SEA SALT; PEPPERMINT OIL; ALCOHOL; GREEN TEA LEAF; STEVIA REBAUDIUNA LEAF; CARVONE, (+/-)-; METHYL SALICYLATE; ECHINACEA ANGUSTIFOLIA LEAF; ASIAN GINSENG; HYDRATED SILICA; GLYCERIN; CARBOXYMETHYLCELLULOSE SODIUM, UNSPECIFIED; CARRAGEENAN; VANILLIN; CRANBERRY SEED OIL; PROPANEDIOL

Directions:

Adults and children 2 years and older:

Brush teeth thoroughly after meals or at least twice a day or use as directed by a dentist.

Do not swallow. To minimize swallowing use a pea-sized amount in children under 6.

Supervise children's brushing until good habits are established.

Children under 2 years ask a dentist.

WARNINGS

Contains sodium fluoride. Children of 6 years and younger: Use a pea-sized amount with supervised brushin to minimize swallowing. In case of intake of fluoride from other sources consult a dentist or doctor.

Active Ingredient: Sodium Fluoride 0.24% (0.14% w/v active fluoride ion) Anticavity

Keep out of reach of children under 6 years of age. If more than used for brushin is accidentally swallowed, get medical help or contact a Poison Control Center right away. Children of 6 years and younger: Use a pea-sized amount with supervised brushin to minimize swallowing. In case of intake of fluoride from other sources consult a dentist or doctor.

PURPOSE

Use: Aids in the prevention of dental cavities.

INACTIVE INGREDIENT

Hydrated Silica, Glycerin, Water, Sorbitol, Sodium Cocoyl Glutamate, Sodium Coco-Sulfate, Sodium Benzoate, MenthaArvensis Leaf Oil, Xanthan Gum, Mentha Piperita (Peppermint Oil), Alcohol, Mica, Carrageenan, Sodium Gluconate, Sodium Hexametaphosphate, Citric Acid, Cocos Nucifera (Coconut) Oil, Disodium Pyophosphate, Stevia Rebaudiana Leaf/Stem Extract, Sucralose, Titanium Dioxide, Carvone, Vanillin, Sodium Sulfate, Gaultheria Procumbens (Wintergreen) Leaf Oil, Vaccinium Macrocarpon (Cranberry) Fruit Extract, Propanediol, Magnesium Chloride, Sea Salt, Camellia Sinensis Extract, Myrciaria Dubia Fruit Extract, Echinacea Angustifolia Leaf Extract, Panax Ginseng Root Extract

INDICATIONS AND USAGE

Children of 6 years and younger: Use a pea sized amount for supervised brushing to minimize swallowing.